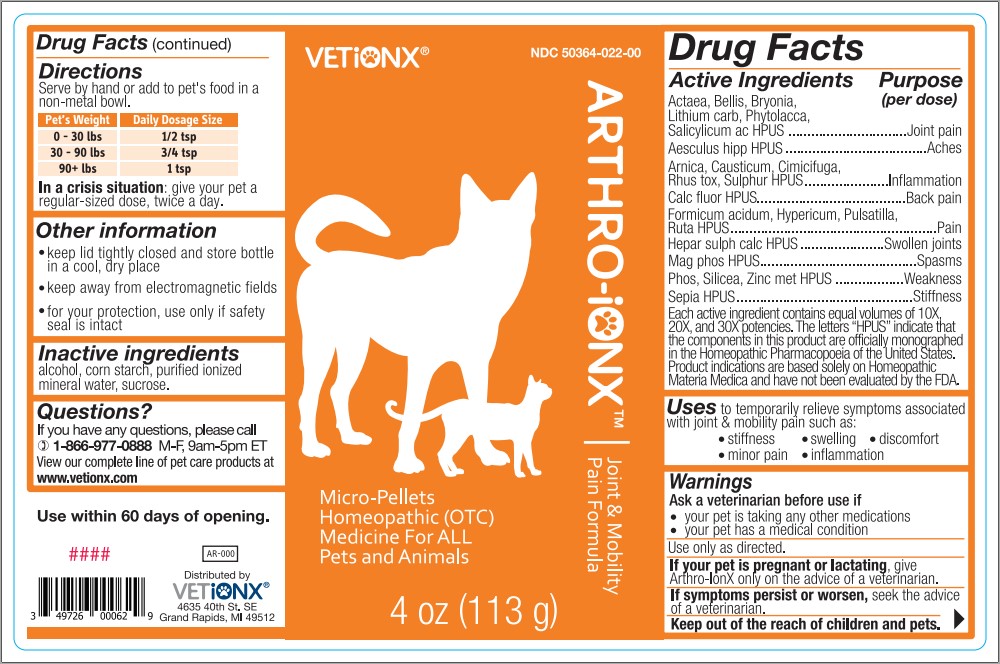 DRUG LABEL: Arthro-Ionx
NDC: 50364-022 | Form: PELLET
Manufacturer: Ionx Health d/b/a VetIonx
Category: homeopathic | Type: OTC ANIMAL DRUG LABEL
Date: 20180410

ACTIVE INGREDIENTS: ACTAEA SPICATA ROOT 10 [hp_X]/113 g; BELLIS PERENNIS 10 [hp_X]/113 g; BRYONIA ALBA ROOT 10 [hp_X]/113 g; LITHIUM CARBONATE 10 [hp_X]/113 g; PHYTOLACCA AMERICANA ROOT 10 [hp_X]/113 g; SALICYLIC ACID 10 [hp_X]/113 g; HORSE CHESTNUT 10 [hp_X]/113 g; ARNICA MONTANA 10 [hp_X]/113 g; CAUSTICUM 10 [hp_X]/113 g; BLACK COHOSH 10 [hp_X]/113 g; TOXICODENDRON PUBESCENS LEAF 10 [hp_X]/113 g; SULFUR 10 [hp_X]/113 g; FORMIC ACID 10 [hp_X]/113 g; HYPERICUM PERFORATUM 10 [hp_X]/113 g; PULSATILLA VULGARIS 10 [hp_X]/113 g; RUTA GRAVEOLENS FLOWERING TOP 10 [hp_X]/113 g; CALCIUM SULFIDE 10 [hp_X]/113 g; MAGNESIUM PHOSPHATE, DIBASIC TRIHYDRATE 10 [hp_X]/113 g; PHOSPHORUS 10 [hp_X]/113 g; SILICON DIOXIDE 10 [hp_X]/113 g; ZINC 10 [hp_X]/113 g; SEPIA OFFICINALIS JUICE 10 [hp_X]/113 g
INACTIVE INGREDIENTS: ALCOHOL; STARCH, CORN; WATER; SUCROSE

ACTIVE INGREDIENT

Actaea, Bellis, Bryonia, Lithium carb, Phytolacca, Salicylicum ac HPUS
Aesculus hipp HPUS
Arnica, Causticum, Cimicifuga, Rhus tox, Sulphur HPUS
Formicum acidum, Hypericum, Pulsatilla, Ruta HPUS
Hepar sulph calc HPUS
Mag phos HPUS
Phos, Silicea, Zinc met HPUS
Sepia HPUS

PURPOSE

Actaea, Bellis, Bryonia, Lithium carb, Phytolacca, Salicylicum ac HPUS...............................Joint pain
Aesculus hipp HPUS.....................................Aches
Arnica, Causticum, Cimicifuga, Rhus tox, Sulphur HPUS......................Inflammation
Formicum acidum, Hypericum, Pulsatilla, Ruta HPUS......................................................Pain
Hepar sulph calc HPUS......................Swollen joints
Mag phos HPUS.........................................Spasms
Phos, Silicea, Zinc met HPUS..................Weakness
Sepia HPUS..............................................Stiffness

Each active ingredient contains equal volumes of 10X, 20X, and 30X potencies. The letters “HPUS” indicate that the components in this product are officially monographed in the Homeopathic Pharmacopoeia of the United States. Product indications are based solely on Homeopathic Materia Medica and have not been evaluated by the FDA.

INDICATIONS AND USAGE

To temporarily relieve symptoms associated with joint & mobility pain such as:

- stiffness
- swelling
- discomfort
- minor pain
- inflammation

WARNINGS

Ask a veterinarian before use if

- your pet is taking any other medication
- your pet has a medical condition

WHEN USING

Use only as directed.

PREGNANCY OR BREAST FEEDING

If your pet is pregnant or lactating, give Arthro-IonX only on the advice of a veterinarian.

ASK DOCTOR

If symptoms persist or worsen, seek the advice of a veterinarian.

KEEP OUT OF REACH OF CHILDREN

Keep out of the reach of children and pets.

DOSAGE AND ADMINISTRATION

Serve by hand or add to pet's food in a non-metal water bowl.

Pet's Weight | Daily Dosage Size
0-30 lbs | 1/2 tsp
30-90 lbs | 3/4 tsp
90+ lbs | 1 tsp

In a crisis situation: give your pet a regular-sized dose, twice a day.

Other Information

- keep lid tightly closed and store bottle in a cool, dry place
- keep away from electromagnetic fields
- for your protection, use only if safety seal is intact

Inactive Ingredients

alcohol, corn starch, purified ionized mineral water, sucrose.

QUESTIONS

If you have any questions, please call 1-866-977-0888 M-F, 9am-5pm ET

View our complet line of pet care products at www.vetionx.com

DESCRIPTION

Use within 60 days of opening.

Distributed by VETiONX

4635 40th St SE

Grand Rapids, MI 49512

PACKAGE LABEL

NDC 50364-022-00

VETiONX

ARTHRO-IONXTM Joint & Mobility Pain Formula

Micro-Pellets Homeopathic (OTC) Medicine for ALL Pets and Animals

4 oz (113 g)